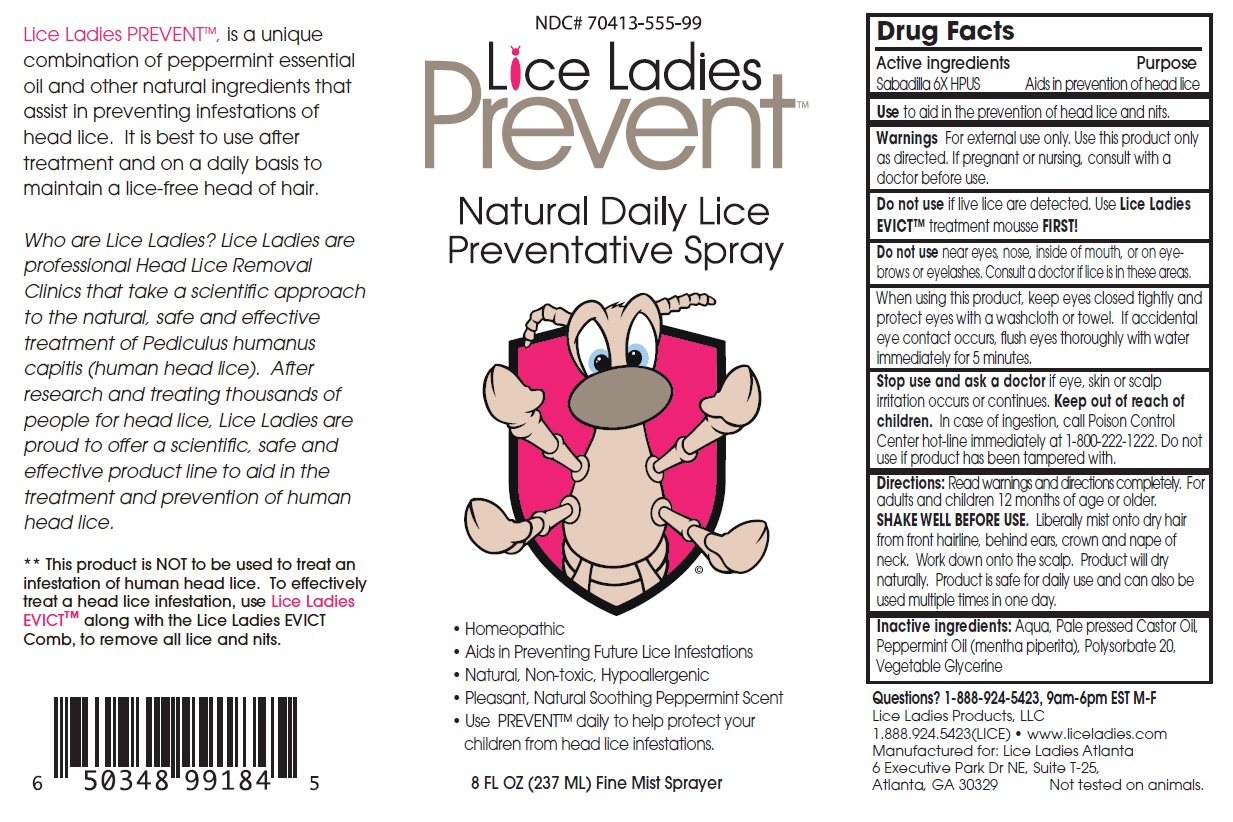 DRUG LABEL: Lice Ladies Prevent
NDC: 70413-555 | Form: SPRAY
Manufacturer: Lice Ladies Atlanta, LLC
Category: homeopathic | Type: HUMAN OTC DRUG LABEL
Date: 20251110

ACTIVE INGREDIENTS: SCHOENOCAULON OFFICINALE SEED 6 [hp_X]/1 mL
INACTIVE INGREDIENTS: WATER; CASTOR OIL; PEPPERMINT OIL; POLYSORBATE 20; GLYCERIN

Lice Ladies Prevent™

Active ingredients

Sabadilla 6X HPUS

Purpose

Aids in prevention of head lice

Use

to aid in the prevention of head lice and nits.

Warnings

For external use only. Use this product only as directed. If pregnant or nursing, consult with a doctor before use.

Do not use if live lice are detected. Use Lice Ladies EVICT™ treatment mousse FIRST!

Do not use near eyes, nose, inside of mouth, or on eyebrows or eyelashes. Consult a doctor if lice is in these areas.

When using this product, keep eyes closed tightly and protect eyes with a washcloth or towel. If accidental eye contact occurs, flush eyes thoroughly with water immediately for 5 minutes.

Stop use and ask a doctor if eye, skin or scalp irritation occurs or continues.

Keep out of reach of children. In case of ingestion, call Poison Control Center hot-line immediately at 1-800-222-1222. Do not use if product has been tampered with.

Directions:

Read warnings and directions completely. For adults and children 12 months of age or older.
SHAKE WELL BEFORE USE. Liberally mist onto dry hair from front hairline, behind ears, crown and nape of neck. Work down onto the scalp. Product will dry naturally. Product is safe for daily use and can also be used multiple times in one day.

Inactive ingredients:

Aqua, Pale pressed Castor Oil, Peppermint Oil (mentha piperita), Polysorbate 20, Vegetable Glycerine

Questions?

1-888-924-5423, 9am-6pm EST M-F

Natural Daily Lice Preventative Spray

• Homeopathic
• Aids in Preventing Future Lice Infestations
• Natural, Non-toxic, Hypoallergenic
• Pleasant, Natural Soothing Peppermint Scent
• Use PREVENT™ daily to help protect your children from head lice infestations.

Fine Mist Sprayer

Lice Ladies Products, LLC
1.888.924.5423(LICE) • www.liceladies.com
Manufactured for: Lice Ladies Atlanta
6 Executive Park Dr NE, Suite T-25,
Atlanta, GA 30329
Not tested on animals.

Lice Ladies PREVENT™, is a unique combination of peppermint essential oil and other natural ingredients that assist in preventing infestations of head lice. It is best to use after treatment and on a daily basis to maintain a lice-free head of hair.

Who are Lice Ladies? Lice Ladies are professional Head Lice Removal Clinics that take a scientific approach to the natural, safe and effective treatment of Pediculus humanus capitis (human head lice). After research and treating thousands of people for head lice, Lice Ladies are proud to offer a scientific, safe and effective product line to aid in the treatment and prevention of human head lice.

** This product is NOT to be used to treat an infestation of human head lice. To effectively treat a head lice infestation, use Lice Ladies EVICT™ along with the Lice Ladies EVICT Comb, to remove all lice and nits.